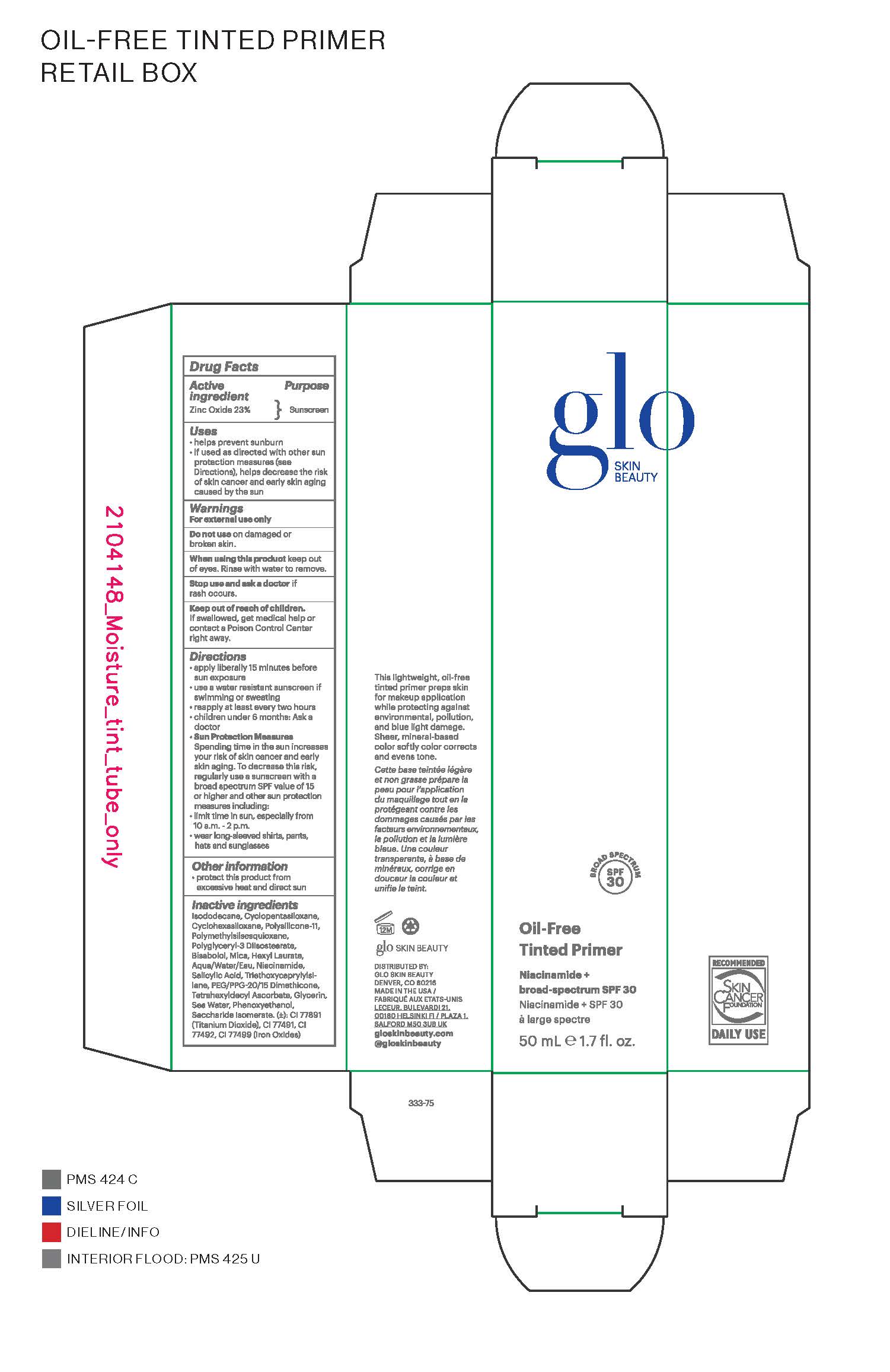 DRUG LABEL: glo SKIN BEAUTY Oil-Free Tinted Primer SPF 30
NDC: 60541-6000 | Form: LOTION
Manufacturer: Hayden Caleel LLC
Category: otc | Type: HUMAN OTC DRUG LABEL
Date: 20250115

ACTIVE INGREDIENTS: ZINC OXIDE 23 g/100 g
INACTIVE INGREDIENTS: ISODODECANE; CYCLOPENTASILOXANE; HEXYL LAURATE; CYCLOHEXASILOXANE; POLYSILICONE-15; POLYMETHYLSILSESQUIOXANE; MICA; BISABOLOL; WATER; TRIETHOXYCAPRYLYLSILANE; PEG/PPG-20/15 DIMETHICONE; NIACINAMIDE; TETRAHEXYLDECYL ASCORBATE; GLYCERIN; POLYGLYCERYL-3 DIISOSTEARATE; PHENOXYETHANOL; SALICYLIC ACID; SACCHARIDE ISOMERATE; TITANIUM DIOXIDE; IRON OXIDES

DRUG FACTS

Active Ingredients

Zinc Oxide 23%

Uses

• helps prevent sunburn • if used as directed with other
sun protection measures (see Directions), decreases the
risk of skin cancer and early skin aging caused by the sun

Warnings

For external use only
Do not use on damaged or broken skin
When using this product keep out of eyes. Rinse with water to remove.
Stop use and ask a docor if rash occurs
Keep out of reach of children. If swalled, get medical help or contact a Poison Control Center right away.

Directions

• apply generously 15 minutes before sun exposure
• reapply at least every 2 hours
• use a water-resistant sunscreen if swimming or sweating
• Sun Protection Measures. Spending time in the sun
increases your risk of skin cancer and early skin aging. To decrease
this risk, regularly use a sunscreen with a Broad Spectrum SPF
value of 15 or higher and other sun protection measures including:
• limit time in the sun, especially from 10 a.m. - 2 p.m.
• wear long-sleeved shirts, pants, hats, and sunglasses
• children under 6 months of age: Ask a doctor

Inactive ingredients

Isododecane, Cyclopentasiloxane, Hexyl Laurate, Cyclohexasiloxane, Polysilicone-11, Polymethylsilsesquioxane, Mica, Bisabolol, Water, Triethoxycaprylylsilane, PEG/PPG-20/15 Dimethicone, Niacinamide, Tetrahexyldecyl Ascorbate, Maris Aqua/Sea Water/Eau de Mer, Glycerin, Polyglyceryl-3 Diisostearate, Phenoxyethanol, Saccharide Isomerate, Salicylic Acid, Titanium Dioxide, Iron Oxides

Other Information

• protect the product in this container from excessive
heat and direct sun

Purpose

Sunscreen

Packaging

Keep out of reach of children